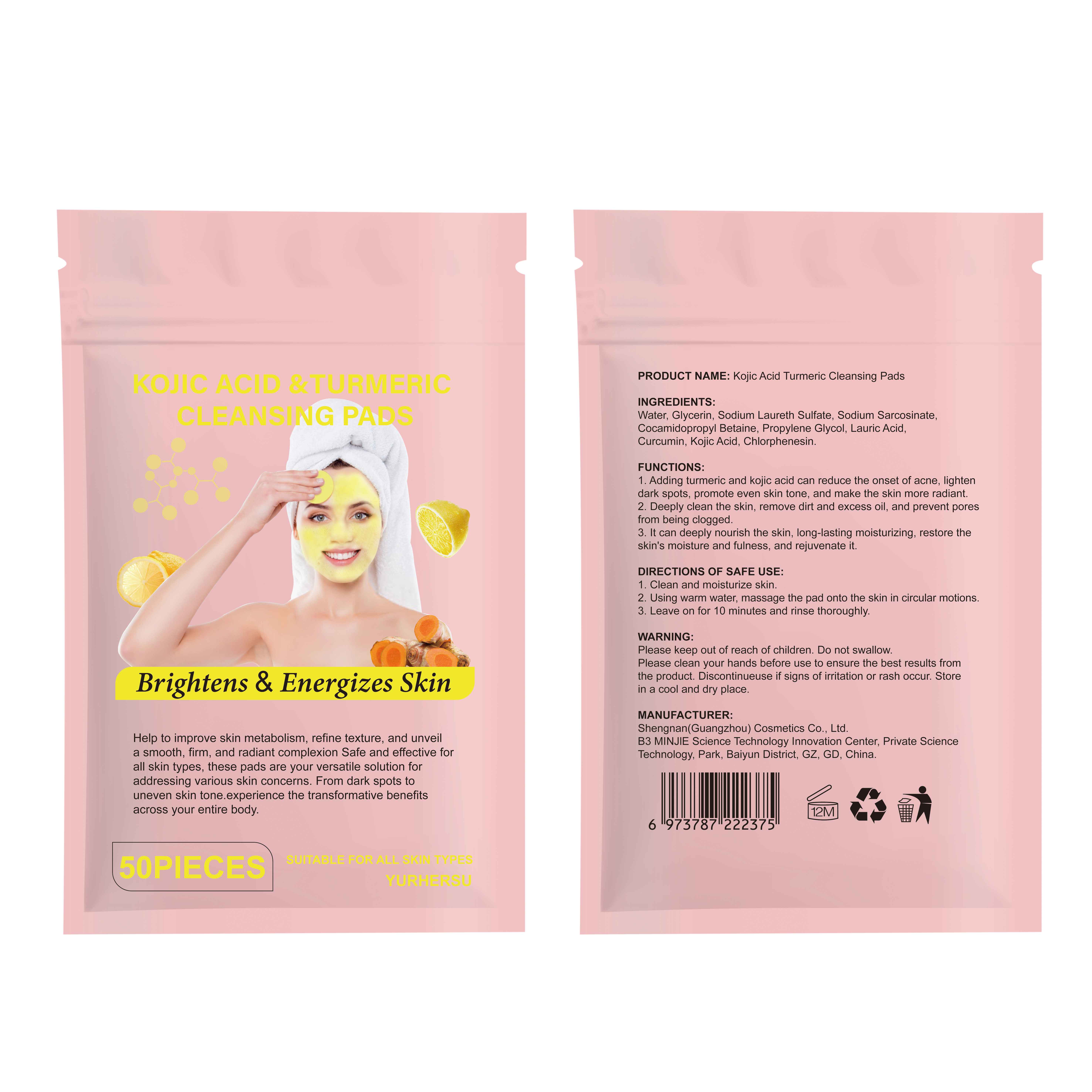 DRUG LABEL: Kojic Acid Turmeric Cleansing Pads
NDC: 84019-015 | Form: CLOTH
Manufacturer: Shengnan (Guangzhou) Cosmetics Co., Ltd
Category: otc | Type: HUMAN OTC DRUG LABEL
Date: 20241213

ACTIVE INGREDIENTS: KOJIC ACID 100 mg/1 g
INACTIVE INGREDIENTS: LAURIC ACID; COCAMIDOPROPYL BETAINE; SODIUM LAURETH SULFATE; CHLORPHENESIN; CURCUMIN; WATER; GLYCERIN; SODIUM SARCOSINATE

Kojic Acid Turmeric Cleansing Pads

WARNINGS

Please keep out of reach of children. Do not swallow.

PURPOSE

Brightens & Energizes

STOP USE

Discontinueuse if signs of irritation or rash occur

ACTIVE INGREDIENT

Kojic Acid

WHEN USING

Please clean your hands before use to ensure the best results fromthe product.

INACTIVE INGREDIENT

WATER
GLYCERIN
SODIUM LAURETH SULFATE
COCAMIDOPROPYL BETAINE
SODIUM SARCOSINATE
PROPYLENE GLYCOL
LAURIC ACID
CURCUMIN
CHLORPHENESIN

DOSAGE AND ADMINISTRATION

Apply 1-3 times a week

INDICATIONS AND USAGE

1.Clean and moisturize skin.
2.Using warm water, massage the pad onto the skin in circular motions.
3. Leave on for 10 minutes and rinse thoroughly.